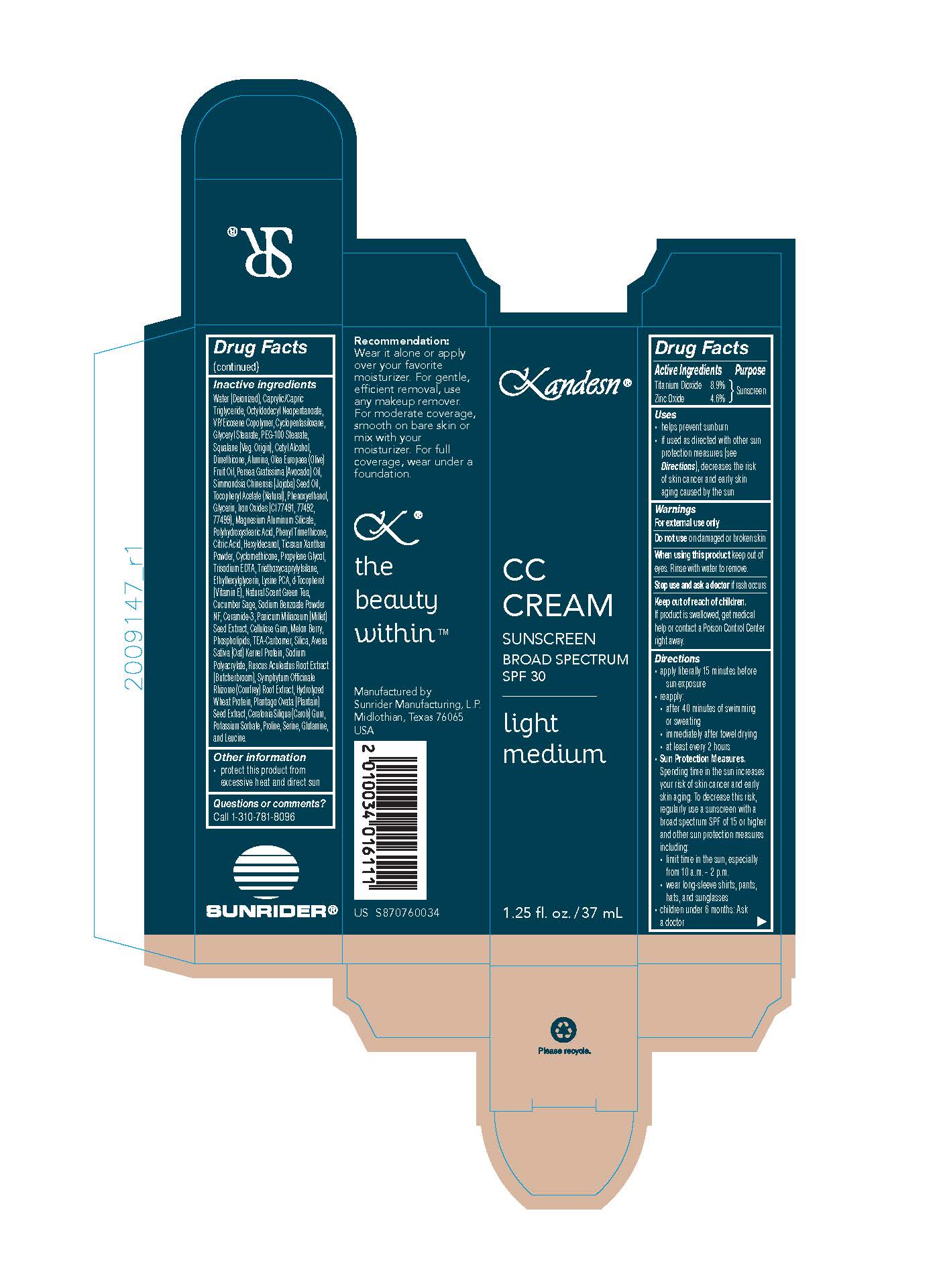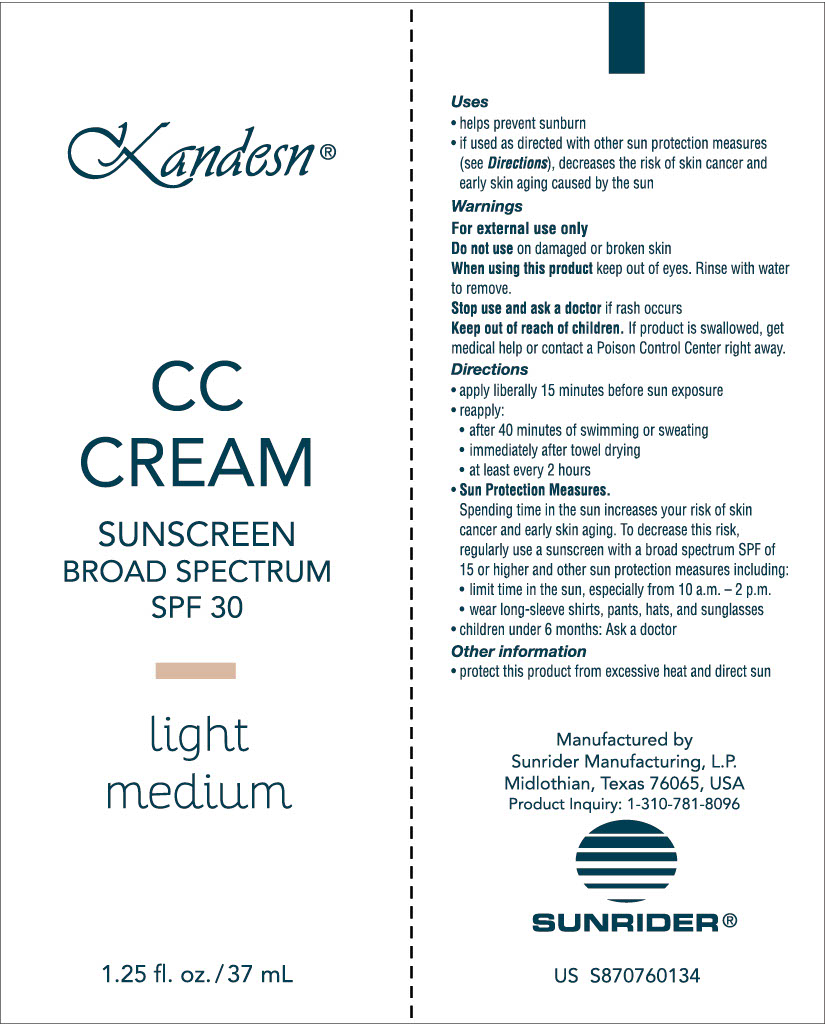 DRUG LABEL: Kandesn CC Cream
NDC: 62191-213 | Form: CREAM
Manufacturer: Sunrider Manufacturing L.P.
Category: otc | Type: HUMAN OTC DRUG LABEL
Date: 20251230

ACTIVE INGREDIENTS: TITANIUM DIOXIDE 114 mg/1 g; ZINC OXIDE 55 mg/1 g
INACTIVE INGREDIENTS: POLYHYDROXYSTEARIC ACID (2300 MW); PHENYL TRIMETHICONE; CITRIC ACID; HEXYLDECANOL; XANTHAN GUM; CYCLOMETHICONE; PROPYLENE GLYCOL; TRISODIUM EDTA; TRIETHOXYCAPRYLYLSILANE; ETHYLHEXYLGLYCERIN; LYSINE PCA; .DELTA.-TOCOPHEROL; GREEN TEA LEAF; SAGE; SODIUM BENZOATE; CERAMIDE 3; MILLET; CELLULOSE GUM; MELON; EGG PHOSPHOLIPIDS; CARBOMER; HYDRATED SILICA; OATMEAL; SODIUM POLYACRYLATE (2500000 MW); RUSCUS ACULEATUS ROOT; COMFREY ROOT; HYDROLYZED WHEAT PROTEIN (ENZYMATIC, 3000 MW); PLANTAGO OVATA SEED; PROLINE; SERINE; GLUTAMINE; LEUCINE; CAROB; POTASSIUM SORBATE; FERRIC OXIDE YELLOW; WATER; CAPRYLIC/CAPRIC TRIGLYCERIDE; OCTYLDODECYL NEOPENTANOATE; VINYLPYRROLIDONE/EICOSENE COPOLYMER; CYCLOPENTASILOXANE; GLYCERYL STEARATE; PEG-100 STEARATE; SQUALANE; CETYL ALCOHOL; DIMETHICONE; ALUMINA; OLEA EUROPAEA (OLIVE) FRUIT OIL; PERSEA GRATISSIMA (AVOCADO) OIL; SIMMONDSIA CHINENSIS (JOJOBA) SEED OIL; ALPHA-TOCOPHEROL ACETATE; PHENOXYETHANOL; GLYCERIN; FERROSOFERRIC OXIDE; MAGNESIUM ALUMINUM SILICATE

Kandesn CC Cream Light Medium

USES:

- helps prevent sunburn
- if used as directed with other sun protection measures (see Directions), decreased the risk of skin cancer and early skin aging caused by the sun.

Directions

- apply liberally 15 minutes before sun exposure
- Reapply:
- after 40 minutes of swimming or sweating
- immediately after towel drying
- at least every 2 hours
- Sun Protection Measures.
- Spending time in the sun increases your risk of skin cancer and early skin aging. To decrease this risk, regularly use a sunscreen with a broad spectrum SPF of 15 or higher and other sun protection measures including:
  - limit time in the sun, expecially from 10 a.m. - 2 p.m.
  - wear long-sleeve shirts, pants, hats, and sunglasses
- children under 6 months: Ask a doctor

Other information

- protect this product from excessive heat and direct sun

ACTIVE INGREDIENTS:

Titanium Dioxide 8.6%
Zinc Oxide 4.6%

INACTIVE INGREDIENT

OTHER INGREDIENTS:

Water (Deionized)
Caprylic/CapricTriglyceride,

Octyldodecyl Neopentanoate,

VP/Eicosene Copolymer,

Cyclopentasiloxane,

Glyceryl Stearate,
PEG-100 Stearate,

Squalane (Veg. Origin),

Cetyl Alcohol,
Dimethicone,

Alumina,
Olea Europaea (Olive) Fruit Oil,

Persea Gratissima (Avocado) Oil,

Simmondsia Chinensis (Jojoba) Seed Oil,

Tocopheryl Acetate (Natural),

Phenoxyethanol,

Glycerin,

Iron Oxides (CI 77491, 77492, 77499),

Magnesium Aluminum Silicate,

Polyhydroxystearic Acid,

Phenyl Trimethicone,

Citric Acid,

Hexyldecanol,

Ticaxan Xanthan Powder,

Cyclomethicone,

Propylene Glycol,

Trisodium EDTA,

Triethoxycaprylylsilane,

Ethylhexylglycerin,

Lysine PCA,

d-Tocopherol (Vitamin E),

Natural Scent Green Tea,

Cucumber Sage,

Sodium Benzoate Powder NF,

Ceramide-3,

Panicum Miliaceum (Millet) Seed Extract,

Cellulose Gum,

Melon Berry,

Phospholipids,

TEA-Carbomer,

Silica,

Avena Sativa (Oat) Kernel Protein,

Sodium Polyacrylate,

Ruscus Aculeatus Root Extract (Butcherbroom),

Symphytum Officinale Rhizome (Comfrey) Root Extract,

Hydrolyzed Wheat Protein,

Plantago Ovata (Plantain) Seed Extract,

Ceratonia Siliqua (Carob) Gum,

Potassium Sorbate,

Proline,

Serine,

Glutamine,

Leucine

WARNINGS:

FOR EXTERNAL USE ONLY

Do not use on damaged or broken skin

When using this product keep out of eyes. Rinse with water to remove.

Stop use and ask a doctor if rash occurs.

Keep out of reach of children.

Keep out of reach of children. If product is swallowed, get medical help or contact a Poison Control Center right away.

KEEP OUT OF REACH OF CHILDREN. If product is swallowed, get medical help or contact a Poison Control Center right away.

Box and Tube Label

Box Tube